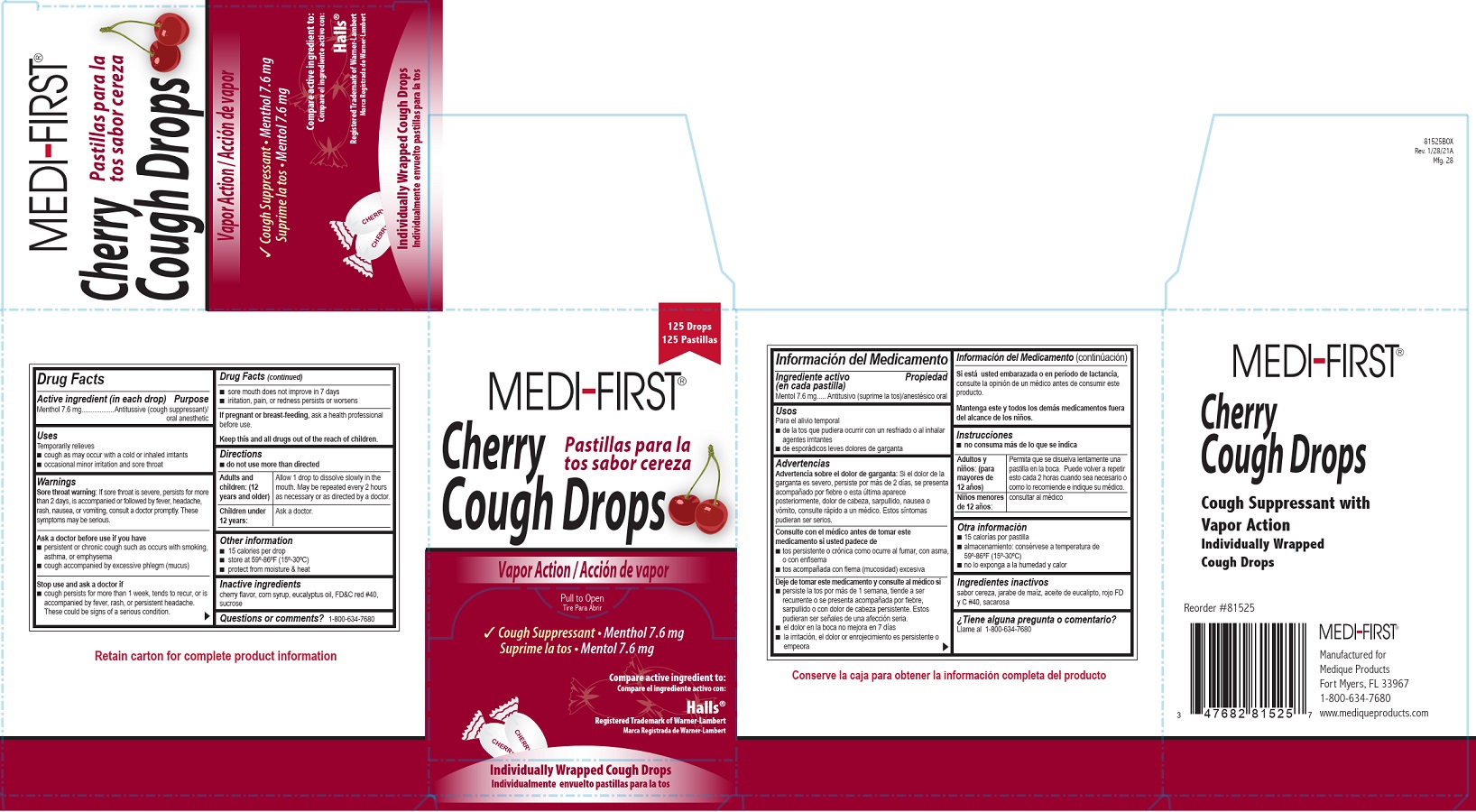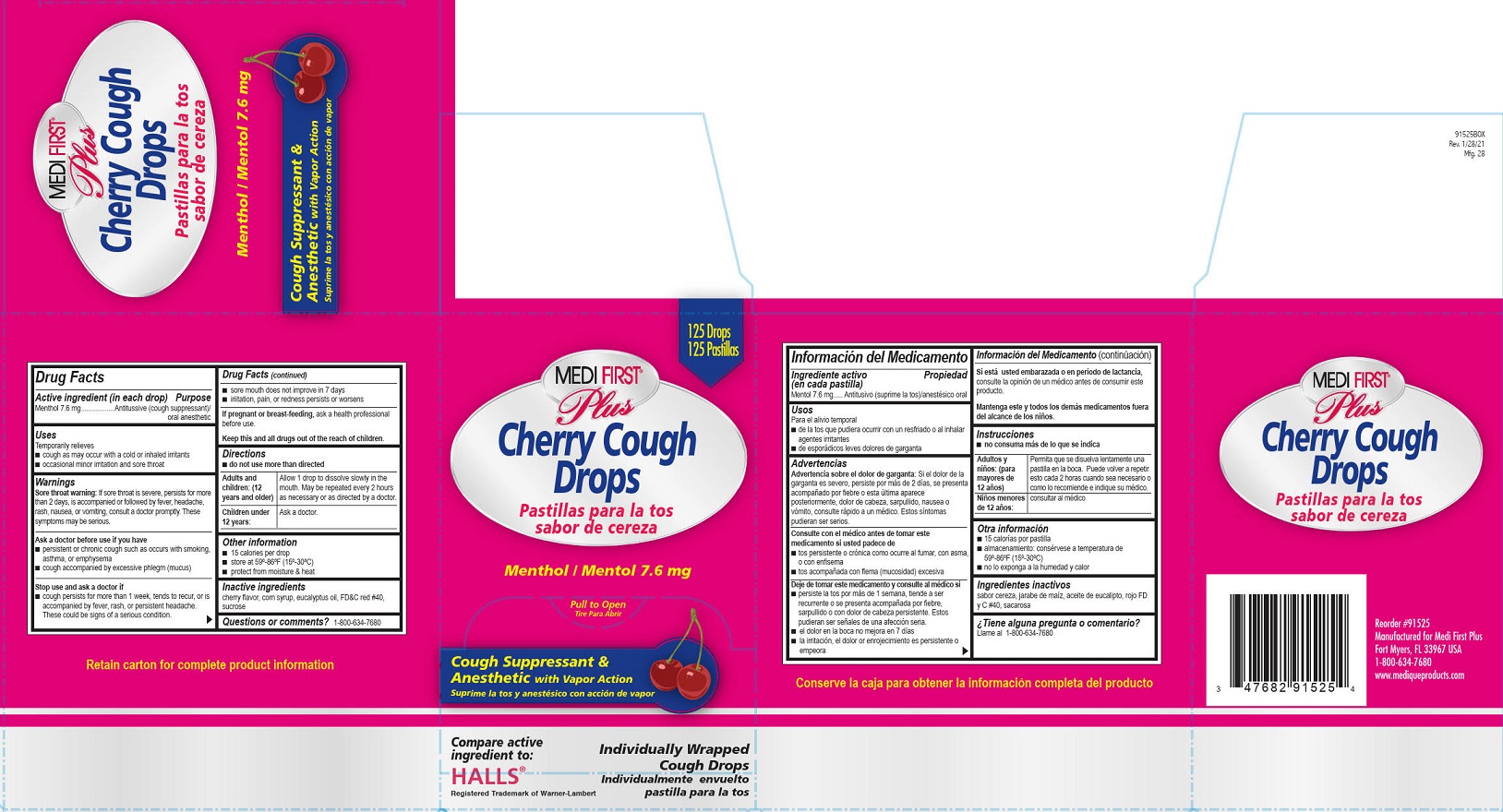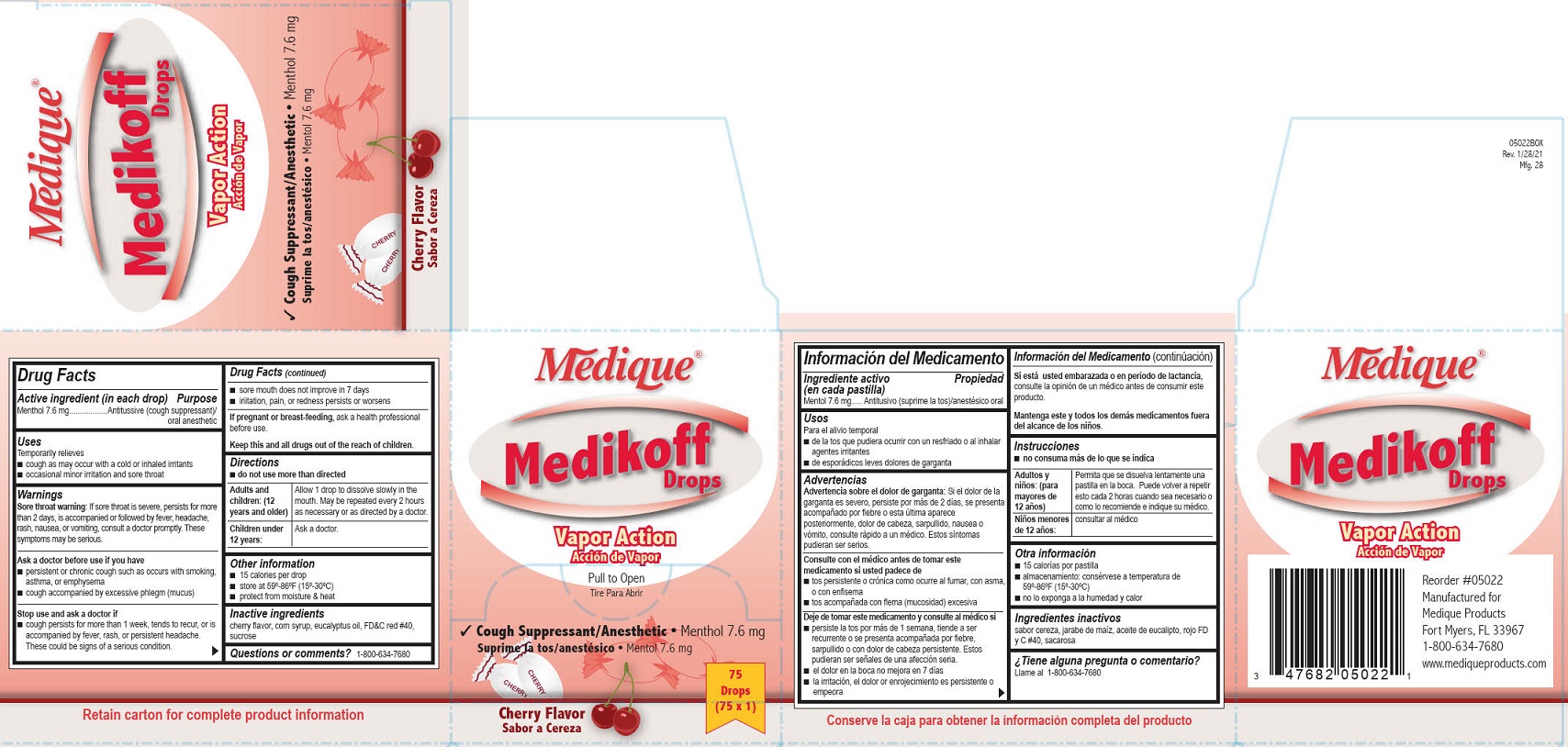 DRUG LABEL: MEDIQUE Medikoff Drops
NDC: 47682-050 | Form: LOZENGE
Manufacturer: Unifirst First Aid Corporation
Category: otc | Type: HUMAN OTC DRUG LABEL
Date: 20250908

ACTIVE INGREDIENTS: MENTHOL 7.6 mg/1 1
INACTIVE INGREDIENTS: CORN SYRUP; EUCALYPTUS OIL; FD&C RED NO. 40; SUCROSE

Cherry Cough Drops

Active ingredient (in each drop)

Menthol 7.6 mg

Purpose

Antitussive (cough suppressant)/oral anesthetic

Uses

Temporarily relieves

■ cough as may occur with a cold or inhaled irritants

■ occasional minor irritation and sore throat

Warnings

Sore throat warning:

If sore throat is severe, persists for more than 2 days, is accompanied or followed by fever, headache, rash, nausea, or vomiting, consult a doctor promptly. These symptoms may be serious.

Ask a doctor before use if you have

■ persistent or chronic cough such as occurs with smoking, asthma, or emphysema

■ cough accompanied by excessive phlegm (mucus)

Stop use and ask a doctor if

■ cough persists for more than 1 week, tends to recur, or is accompanied by fever, rash, or persistent
headache. These could be signs of a serious condition.

■ sore mouth does not improve in 7 days

■ irritation, pain, or redness persists or worsens

PREGNANCY OR BREAST FEEDING

If pregnant or breast-feeding, ask a health professional before use.

KEEP OUT OF REACH OF CHILDREN

Keep this and all drugs out of the reach of children.

Directions

- do not use more than directed

Adults and children:
(12 years and older)

Allow 1 drop to dissolve slowly in the mouth. May be repeated every 2 hours as necessary or as directed by a doctor.

Children under 12 years:

Ask a doctor

Other information

- 15 calories per drop
- store at 59-86°F (15°-30°C)
- protect from moisture & heat

Inactive ingredients

cherry flavor, corn syrup, eucalyptus oil, FD&C red #40, sucrose

Questions or comments? 1-800-634-7680

Medi-First Cherry Cough Drop Box Label

Medi-First ® Cherry Cough Drops

Pastillas parala tos sabor cereza

Vapor Action/accion de vapor
Pull to Open
Tire Para Abrir
Cough Suppressant/Oral Anethestic Menthol 7.6mg
Suprime la tos/Anestesico Mentol 7.6mg
Compare active ingredient to:
Compare el ingrediente activo con:
Halls ® Registered Trademark of Warner-Lambert
Marca Registrada de WarnerLambert
IndividuallyWrapped Cough Drops
Individualmente Envuelto para la tos

125 Drops

125 Pastillas

Medi-First Plus Cherry Cough Drop Label

125 Drops
125 Pastillas
Medi First® Plus

Cherry Cough Drops
Pastillas para la tos sabor cereza

Menthol/Mentol 7.6 mg
Pull To Open

Tire Para Abrir
Cough Suppressant and Anesthetic with Vapor Action
Suprime la tos y anestesico con accion de vapor
Compare active ingredient to:
Halls® Registered Trademark of Warner-Lambert
IndividuallyWrapped Cough Drops
Individualmente envuelto pastilla para la tos

Medique Medikoff Label

Medique®
Medikoff Drops
Vapor Action

Accion de Vapor

Cough Suppressant/Anesthetic • Menthol 7.6mg

Suprima la tos/anestesico • Mentol 7.6 mg

75
Drops
(75 x 1)